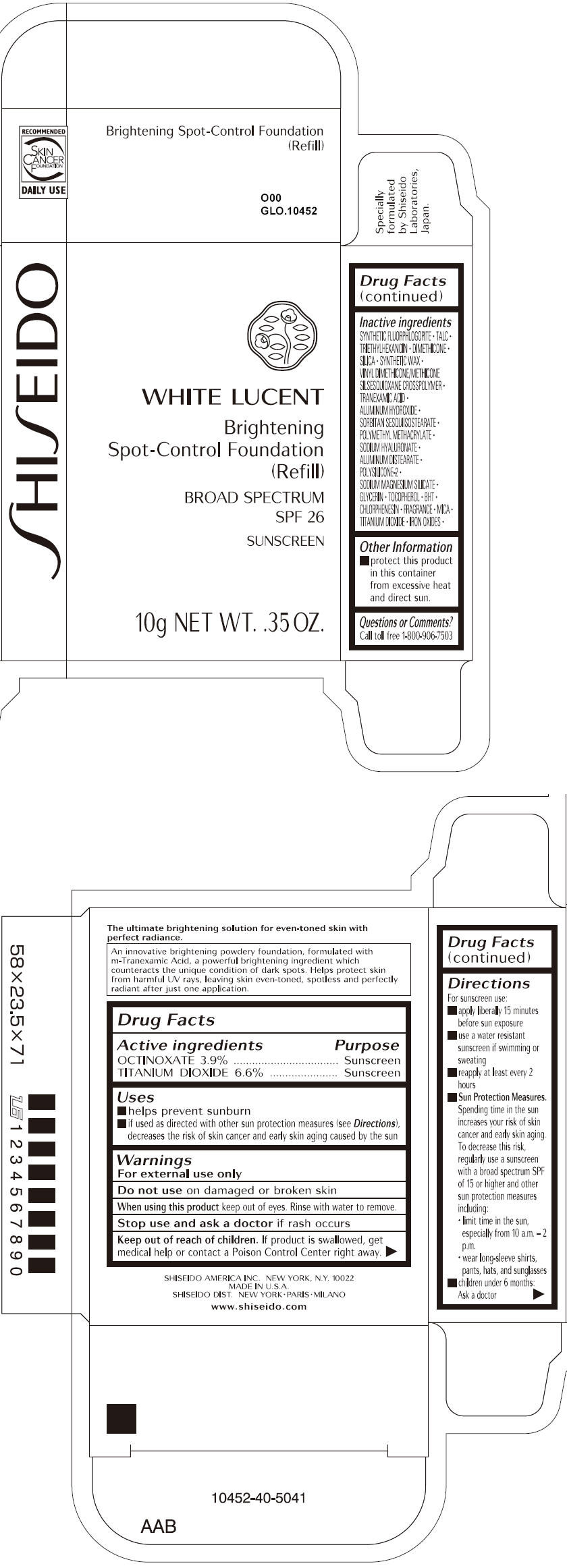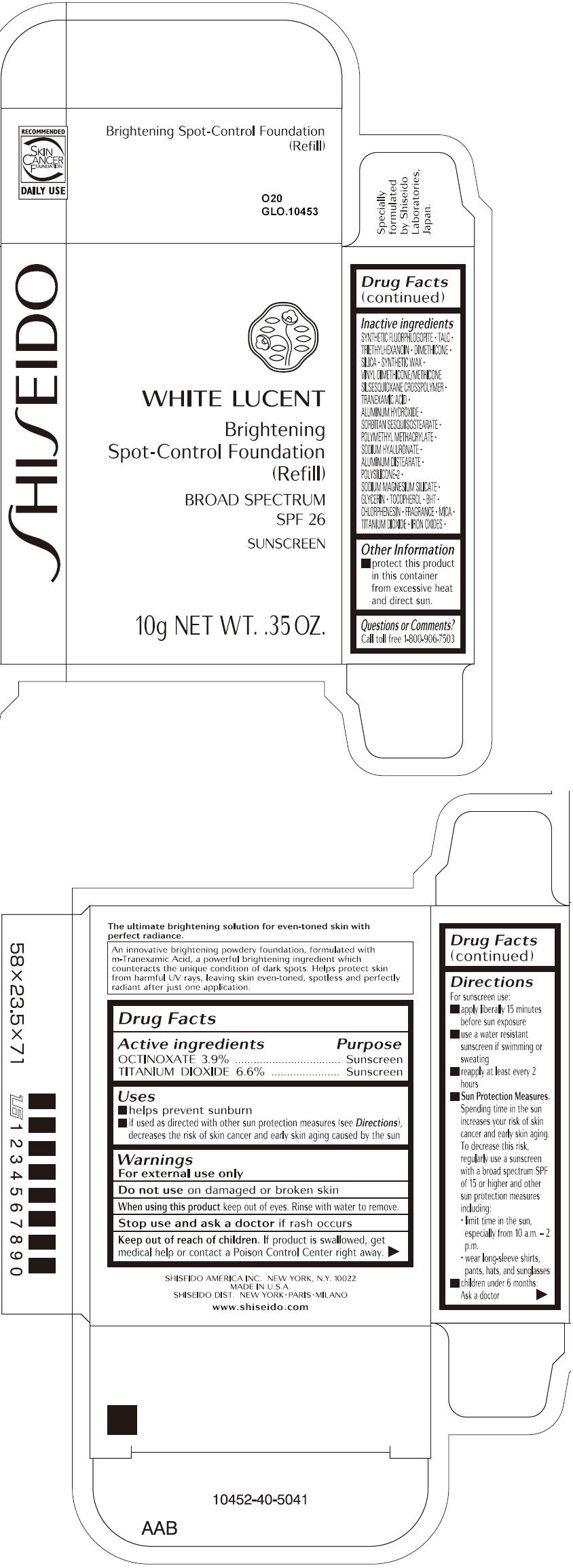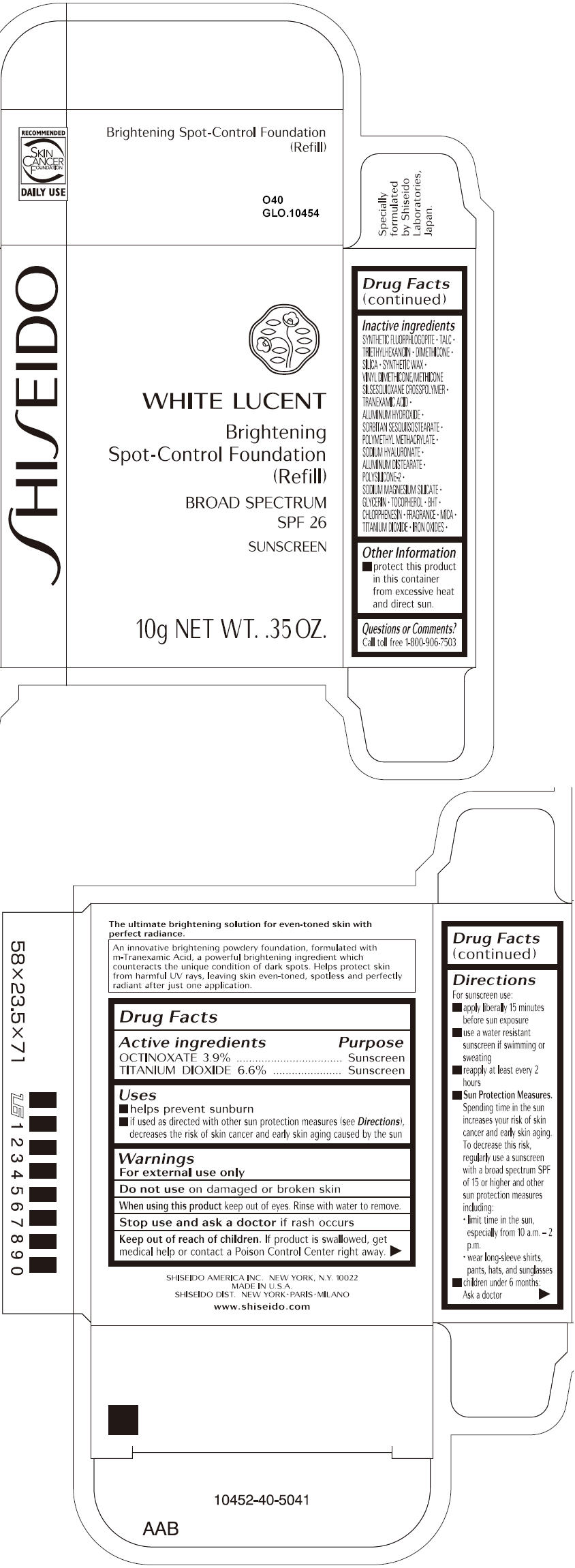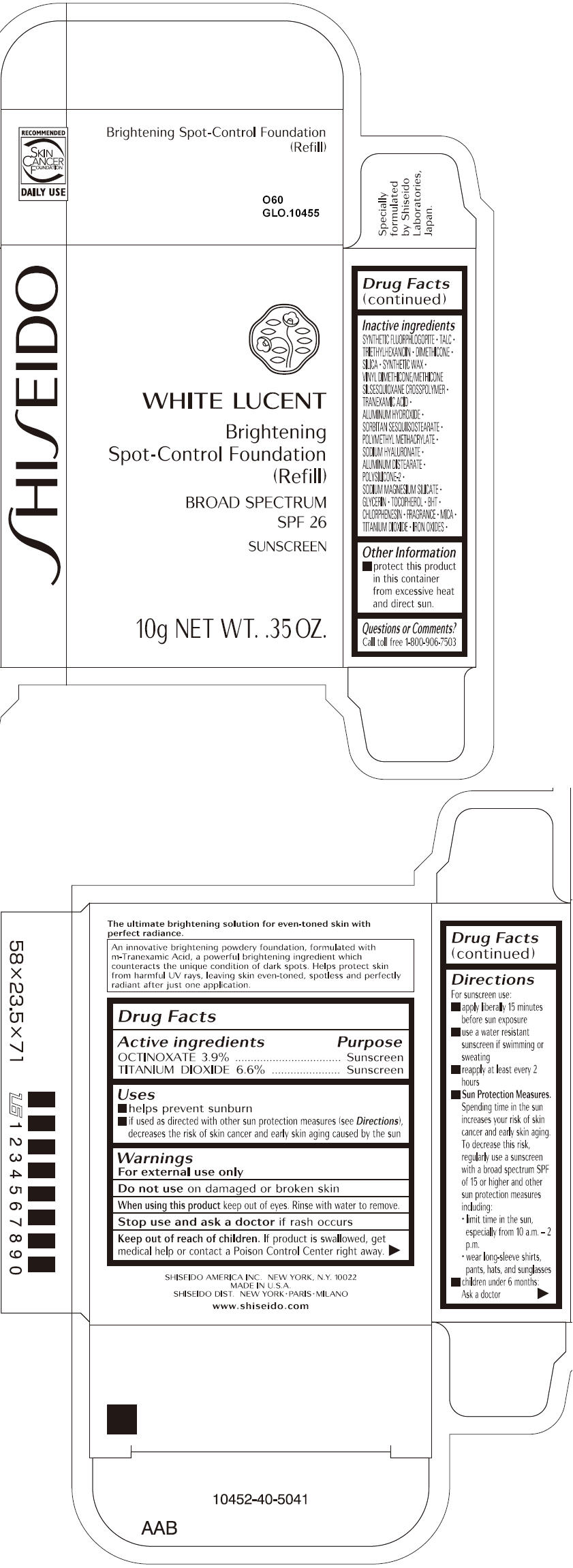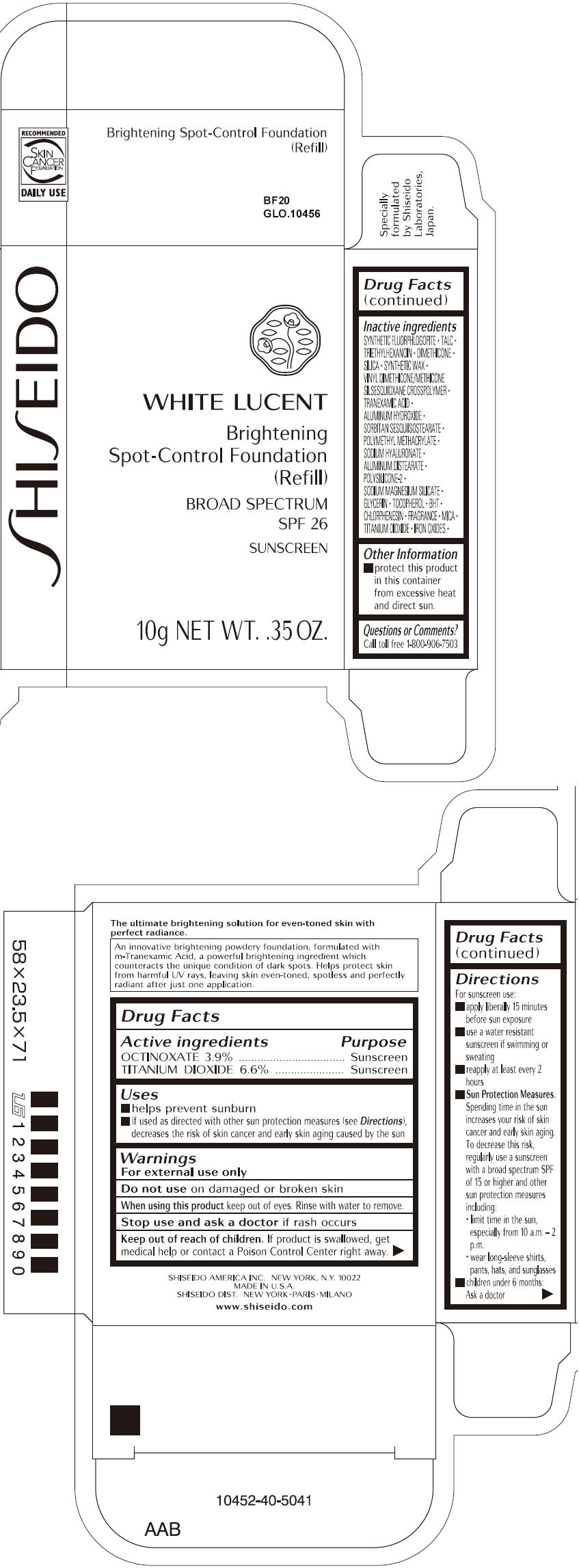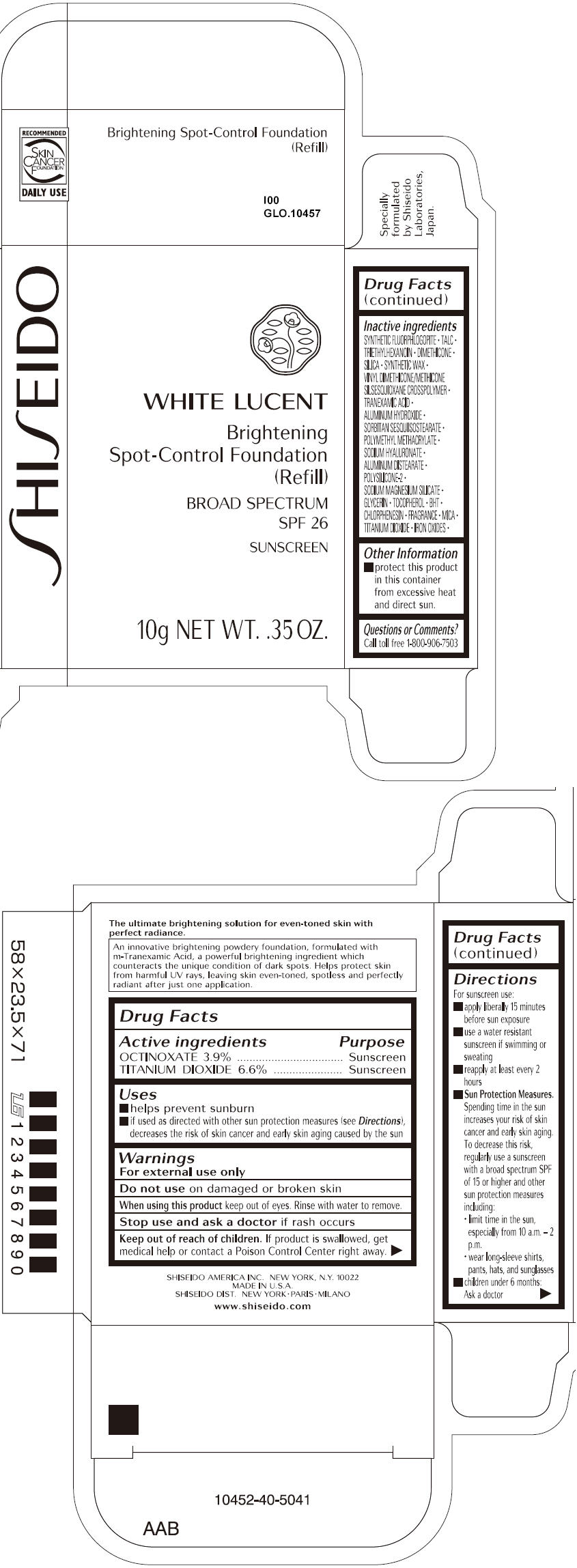 DRUG LABEL: SHISEIDO WHITE LUCENT BRIGHTENING SPOT-CONTROL FOUNDATION (REFILL) 
NDC: 52686-252 | Form: PASTE
Manufacturer: SHISEIDO AMERICA INC.
Category: otc | Type: HUMAN OTC DRUG LABEL
Date: 20230927

ACTIVE INGREDIENTS: OCTINOXATE 0.39 g/10 g; TITANIUM DIOXIDE 0.66 g/10 g
INACTIVE INGREDIENTS: MICA; TALC; TRIETHYLHEXANOIN; DIMETHICONE; FERRIC OXIDE RED; FERROSOFERRIC OXIDE; FERRIC OXIDE YELLOW; SYNTHETIC WAX (1200 MW); SILICON DIOXIDE; TRANEXAMIC ACID; ALUMINUM HYDROXIDE; ALUMINUM DISTEARATE; CHLORPHENESIN; GLYCERIN; .ALPHA.-TOCOPHEROL; BUTYLATED HYDROXYTOLUENE; HYALURONATE SODIUM

SHISEIDO WHITE LUCENT BRIGHTENING SPOT-CONTROL FOUNDATION (REFILL)

Drug Facts

ACTIVE INGREDIENT

ACTIVE INGREDIENTS: | Purpose
OCTINOXATE 3.9% | Sunscreen
TITANIUM DIOXIDE 6.6% | Sunscreen

Uses

- helps prevent sunburn
- if used as directed with other sun protection measures (see Directions), decreases the risk of skin cancer and early skin aging caused by the sun

Warnings

For external use only

Do not use on damaged or broken skin

When using this product keep out of eyes. Rinse with water to remove.

Stop use and ask a doctor if rash occurs

Keep out of reach of children. If product is swallowed, get medical help or contact a Poison Control Center right away.

Directions

For sunscreen use:

- apply liberally 15 minutes before sun exposure
- use a water resistant sunscreen if swimming or sweating
- reapply at least every 2 hours
- Sun Protection Measures. Spending time in the sun increases your risk of skin cancer and early skin aging. To decrease this risk, regularly use a sunscreen with a broad spectrum SPF of 15 or higher and other sun protection measures including:
  - limit time in the sun, especially from 10 a.m. – 2 p.m.
  - wear long-sleeve shirts, pants, hats, and sunglasses
- children under 6 months: Ask a doctor

Inactive Ingredients

SYNTHETIC FLUORPHLOGOPITE, TALC, TRIETHYLHEXANOIN, DIMETHICONE, SILICA, SYNTHETIC WAX, VINYL DIMETHICONE/METHICONE SILSESQUIOXANE CROSSPOLYMER, TRANEXAMIC ACID, ALUMINUM HYDROXIDE, SORBITAN SESQUIISOSTEARATE, POLYMETHYL METHACRYLATE, SODIUM HYALURONATE, ALUMINUM DISTEARATE, POLYSILICONE-2, SODIUM MAGNESIUM SILICATE, GLYCERIN, TOCOPHEROL, BHT, CHLORPHENESIN, FRAGRANCE, MICA, TITANIUM DIOXIDE, IRON OXIDES,

Other information

- protect this product in this container from excessive heat and direct sun.

Questions or comments?

Call toll free 1-800-906-7503

SHISEIDO AMERICA INC. NEW YORK, N.Y. 10022
SHISEIDO DIST. NEW YORK • PARIS • MILANO

PRINCIPAL DISPLAY PANEL - 10g Tray Carton - O00

SHISEIDO

WHITE LUCENT

Brightening
Spot-Control Foundation
(Refill)

BROAD SPECTRUM
SPF 26

SUNSCREEN

10g NET WT. .35 OZ.

PRINCIPAL DISPLAY PANEL - 10g Tray Carton - O20

SHISEIDO

WHITE LUCENT

Brightening
Spot-Control Foundation
(Refill)

BROAD SPECTRUM
SPF 26

SUNSCREEN

10g NET WT. .35 OZ.

PRINCIPAL DISPLAY PANEL - 10g Tray Carton - O40

SHISEIDO

WHITE LUCENT

Brightening
Spot-Control Foundation
(Refill)

BROAD SPECTRUM
SPF 26

SUNSCREEN

10g NET WT. .35 OZ.

PRINCIPAL DISPLAY PANEL - 10g Tray Carton - O60

SHISEIDO

WHITE LUCENT

Brightening
Spot-Control Foundation
(Refill)

BROAD SPECTRUM
SPF 26

SUNSCREEN

10g NET WT. .35 OZ.

PRINCIPAL DISPLAY PANEL - 10g Tray Carton - BF20

SHISEIDO

WHITE LUCENT

Brightening
Spot-Control Foundation
(Refill)

BROAD SPECTRUM
SPF 26

SUNSCREEN

10g NET WT. .35 OZ.

PRINCIPAL DISPLAY PANEL - 10g Tray Carton - I00

SHISEIDO

WHITE LUCENT

Brightening
Spot-Control Foundation
(Refill)

BROAD SPECTRUM
SPF 26

SUNSCREEN

10g NET WT. .35 OZ.